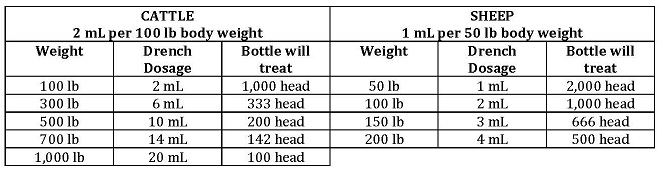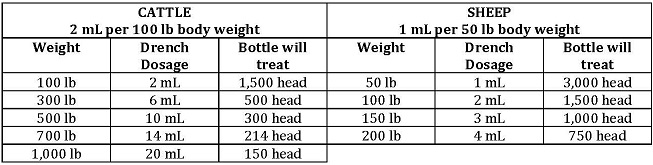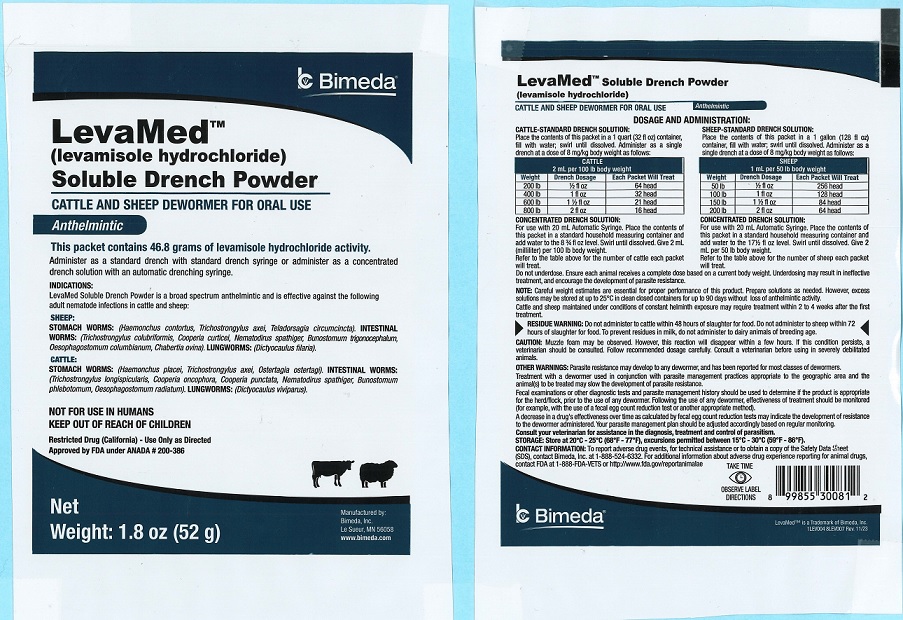 DRUG LABEL: LevaMed Soluble Drench Powder
NDC: 61133-0270 | Form: POWDER
Manufacturer: Bimeda, Inc.
Category: animal | Type: OTC ANIMAL DRUG LABEL
Date: 20241205

ACTIVE INGREDIENTS: LEVAMISOLE HYDROCHLORIDE 46.8 g/52 g

DESCRIPTION

LevaMedTM
(levamisole hydrochloride)
Soluble Drench Powder
CATTLE AND SHEEP DEWORMER FOR ORAL USE
Anthelmintic

HOW SUPPLIED

The 52 g packet contains 46.8 grams of levamisole hydrochloride activity.
The 403 g bottle contains 362.7 grams of levamisole hydrochloride activity.
The 605 g bottle contains 544.5 grams of levamisole hydrochloride activity.
Administer as a standard drench with standard drench syringe or administer as a concentrated drench solution with an automatic drenching syringe.

INDICATIONS:
LevaMed (levamisole hydrochloride) Soluble Drench Powder is a broad spectrum anthelmintic and is effective against the following adult nematode infections in cattle and sheep:
SHEEP:
STOMACH WORMS: (Haemonchus contortus, Trichostrongylus axei, Teladorsagia circumcincta).INTESTINAL WORMS: (Trichostrongylus colubriformis, Cooperia curticei, Nematodirus spathiger, Bonostomum trigoncephalum, Oesophagostomum columbianum, Chabertia ovina), LUNGWORMS:(Dictyocaulus filaria).

CATTLE:
STOMACH WORMS:(Haemonchus placei, Trichostrongylus axei, Ostertagia ostertagi). INTESTINAL WORMS: (Trichostrongylus longispicularis, Cooperia oncophora, Cooperia punctata, Nematodirus spathiger, Bunostomum phlebotomum, Oesophagostomum radiatum), LUNGWORMS: (Dictyocaulus viviparus).

NOT FOR USE IN HUMANS
KEEP OUT OF REACH OF CHILDREN
Restricted Drug (California) - Use Only as Directed
Approved by FDA under ANADA # 200-386

DOSAGE AND ADMINISTRATION

52 g pouch

CATTLE-STANDARD DRENCH SOLUTION:

Place the contents of this packet in a 1 quart (32 fl oz) container, fill with water; swirl until dissolved. Administer as a single drench at a dose of 8 mg/kg body weight as follows:

Weight | Drench Dosage | Each Packet Will Treat
200 lb | 1/2 fl oz | 64 head
400 lb | 1 fl oz | 32 head
600 lb | 1 1/2 fl oz | 21 head
800 lb | 2 fl oz | 16 head

CONCENTRATED DRENCH SOLUTION:

For use with 20 mL Automatic Syringe. Place the contents of this packet in a standard household measuring container and add water to the 8 3/4 fl oz level. Swirl until dissolved. Give 2 mL (milliliter) per 100 lb body weight. Refer to the table above for the number of cattle each packet will treat.

SHEEP-STANDARD DRENCH SOLUTION:
Place the contents of this packet in a 1 gallon (128 fl oz) container, fill with water; swirl until dissolved. Administer as a single drench at a dose of 8 mg/kg body weight as follows:

Weight | Drench Dosage | Each Package Will Treat
50 lb | 1/2 fl oz | 256 head
100 lb | 1 fl oz | 128 head
150 lb | 1 1/2 fl oz | 84 head
200 lb | 2 fl oz | 64 head

CONCENTRATED DRENCH SOLUTION:
For use with 20 mL Automatic Syringe. Place the contents of this packet in a standard household measuring container and add water to the 17 1/2 fl oz level. Swirl until dissolved. Give 2 mL per 50 lb body weight. Refer to the table above for the number of sheep each packet will treat.

Prepare solutions as needed. However excess solutions may be stored at up to 25°C in clean closed containers for up to 90 days without loss of anthelmintic activity.

DOSAGE AND ADMINISTRATION
403 g
When you are ready to deworm your cattle or sheep, add 2 liters of water to the solution in this bottle.
Swirl to mix thoroughly before using. If any solution is left over, it may be stored at up to 25°C for up to 3 months in this tightly capped bottle. Shake well before using.

Month ______ Day _______ Year _______
Administer as a single drench at a dose of 8 mg/kg body weight as follows:

DOSAGE AND ADMINISTRATION

605 g
When you are ready to deworm your cattle or sheep, add 3 liters of water to the solution in this bottle.
Swirl to mix thoroughly before using. If any solution is left over, it may be stored at up to 25°C for up to 3 months in this tightly capped bottle. Shake well before using.

Month ______ Day _______ Year _______
Administer as a single drench at a dose of 8 mg/kg body weight as follows:

Do not underdose. Ensure each animal receives a complete dose based on a current body weight. Underdosing may result in ineffective treatment, and encourage the development of parasite resistance.

NOTE: Careful weigh estimates are essential for proper performance of this product.

Cattle and sheep maintained under conditions of constant helminth exposure may require treatment within 2 to 4 weeks after the first treatment.

RESIDUE WARNING

RESIDUE WARNING: Do not administer to cattle within 48 hours of slaughter for food. Do not administer to sheep within 72 hours of slaughter for food. To prevent residues in milk, do not administer to dairy animals of breeding age.

PRECAUTIONS

CAUTION: Muzzle foam may be observed. However, this reaction will disappear within a few hours. If this condition persists, a veterinarian should be consulted. Follow recommended dosage carefully. Consult a veterinarian before using in severely debilitated animals.

WARNINGS

OTHER WARNINGS: Parasite resistance may develop to any dewormer, and has been reported for most classes of dewormers.

Treatment with a dewormer used in conjunction with parasite management practices appropriate to the geographic area and the animal(s) to be treated may slow the development of parasite resistance.

Fecal examinations or other diagnostic tests and parasite management history should be used to determine if the product is appropriate for the herd/flock, prior to the use of any dewormer. Following the use of any dewormer, effectiveness of treatment should be monitored (for example, with the use of a fecal egg count reduction test or another appropriate method).

A decrease in a drug's effectiveness over time as calculated by fecal egg count reduction tests may indicate the development of resistance to the dewormer administered. Your parasite management plan should be adjusted accordingly based on regular monitoring.

Consult your veterinarian for assistance in the diagnosis, treatment and control of parasitism.

STORAGE AND HANDLING

STORAGE: Store at 20°C-25°C (68°F-77°F), excursions permitted between 15°C-30°C (59°F-86°F).

CONTACT INFORMATION: To report adverse drug events, for technical assistance or to obtain a copy of the Safety Data Sheet (SDS), contact Bimeda, Inc. at 1-888-524-6332. For additional information about adverse drug experience reporting for animal drugs, contact FDA at 1-888-FDA-VETS or http://www.fda.gov/reportanimalae